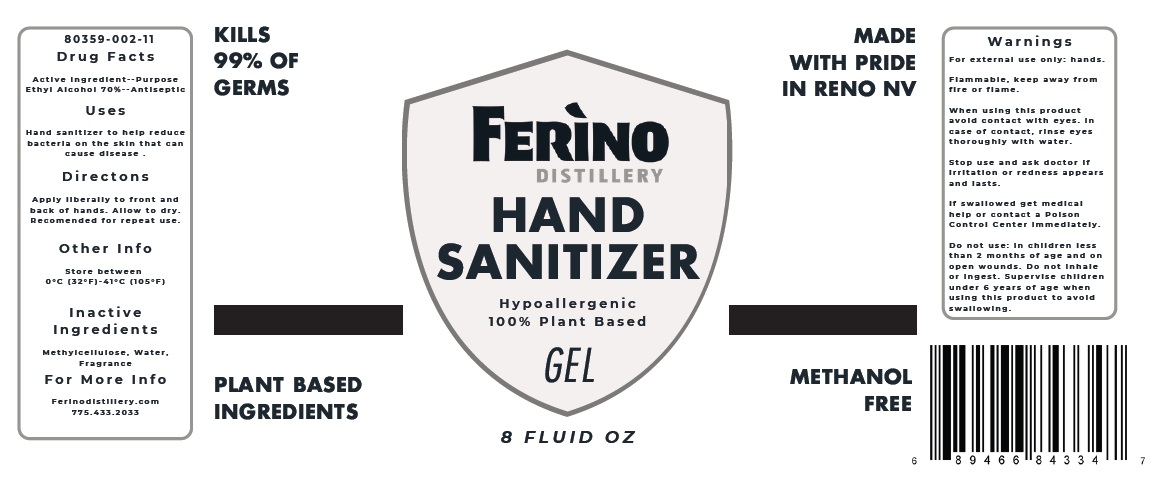 DRUG LABEL: Ferino Hand Sanitizer
NDC: 80359-002 | Form: GEL
Manufacturer: Ferino Distillery
Category: otc | Type: HUMAN OTC DRUG LABEL
Date: 20201014

ACTIVE INGREDIENTS: ALCOHOL 70 mL/100 mL
INACTIVE INGREDIENTS: METHYLCELLULOSE, UNSPECIFIED; WATER

FERINO DISTILLERY HAND SANITIZER GEL

Active Ingredient

Ethyl Alcohol 70%

Purpose

Antiseptic

Uses

Hand sanitizer to help reduce bacteria on the skin that can cause disease.

Directions

Apply liberally to front and back of hands. Allow to dry. Recommended for repeat use.

Other Info

Store between 0° C (32° F) - 41° C (105° F)

Inactive Ingredients

Methylcellulose, Water, Fragrance

For More Info

Ferinodistillery.com

775.433.2033

Warnings

For external use only: hands.

Flammable, keep away from fire or flame.

When using this product avoid contact with eyes. In case of contact, rinse eyes thoroughly with water.

Stop use and ask doctor if irritation or redness appears and lasts.

KEEP OUT OF REACH OF CHILDREN

If swallowed get medical help or contact a Poison Control Center immediately.

Do not use: in children less than 2 months of age and open wounds. Do not inhale or ingest. Supervise children under 6 years of age when using this product to avoid swallowing.

Hypoallergenic

100% Plant Based

KILLS 99% OF GERMS

PLANT BASED INGREDIENTS

MADE WITH PRIDE IN RENO NV

METHANOL FREE